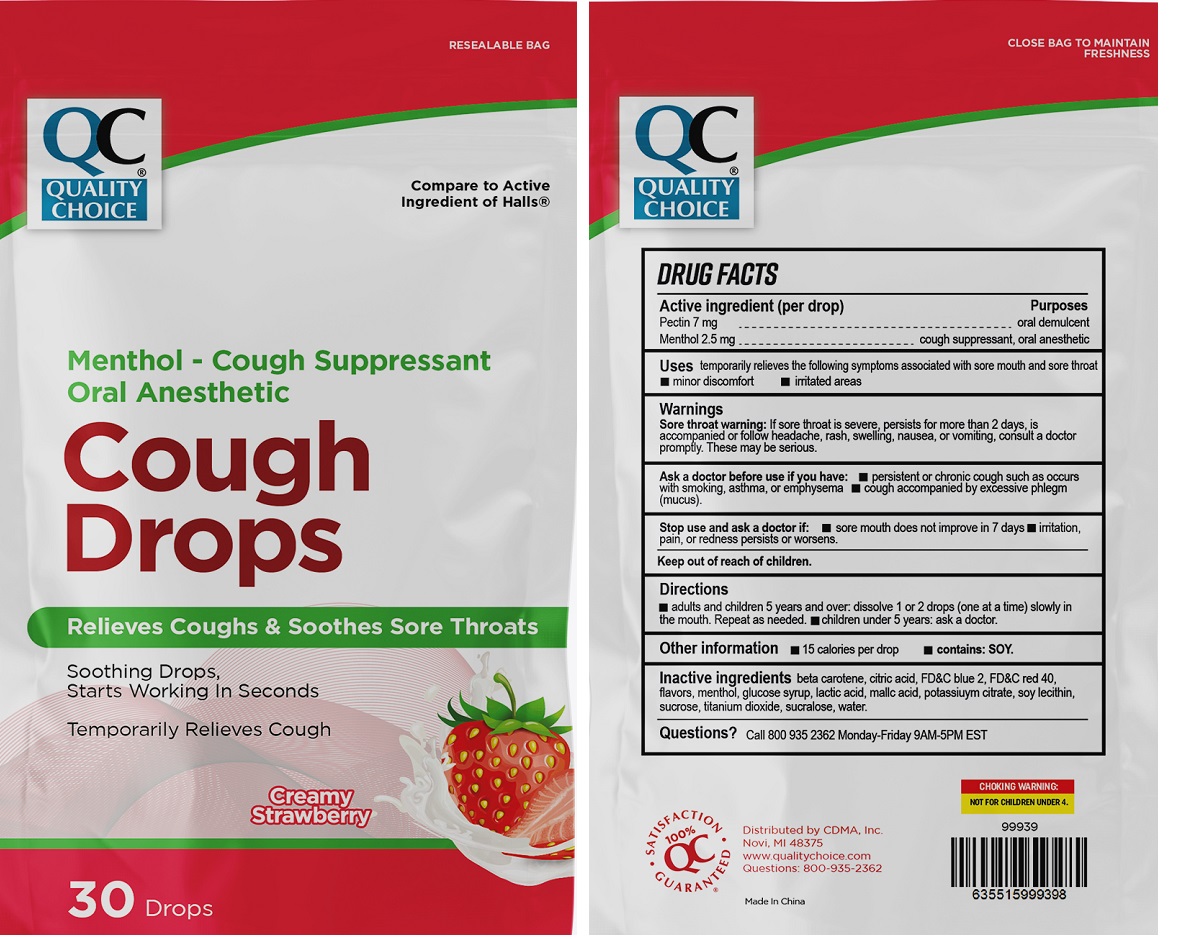 DRUG LABEL: QUALITY CHOICE Cough Drops Creamy Strawberry
NDC: 83698-625 | Form: LOZENGE
Manufacturer: Xiamen Kang Zhongyuan Biotechnology Co., Ltd.
Category: otc | Type: HUMAN OTC DRUG LABEL
Date: 20251229

ACTIVE INGREDIENTS: PECTIN 7 mg/1 1; MENTHOL, UNSPECIFIED FORM 2.5 mg/1 1
INACTIVE INGREDIENTS: BETA CAROTENE; CITRIC ACID MONOHYDRATE; FD&C BLUE NO. 2; FD&C RED NO. 40; CORN SYRUP; LACTIC ACID, UNSPECIFIED FORM; MALIC ACID; POTASSIUM CITRATE; SOYBEAN LECITHIN; SUCROSE; TITANIUM DIOXIDE; SUCRALOSE; WATER

QUALITY CHOICE®Cough Drops Creamy Strawberry

Active ingredient (per drop)

Pectin 7 mg
Menthol 2.5 mg

Purposes

oral demulcent
cough suppressant, oral anesthetic

Uses

temporarily relieves the following symptoms associated with sore mouth and sore throat
• minor discomfort • irritated areas

Warnings

Sore throat warning:If sore throat is severe, persists for more than 2 days, is accompanied or follow headache, rash, swelling, nausea, or vomiting, consult a doctor promptly. These may be serious.

Ask a doctor before use if you have:• persistent or chronic cough such as occurs with smoking, asthma, or emphysema • cough accompanied by excessive phlegm (mucus).

Stop use and ask a doctor if:• sore mouth does not improve in 7 days • irritation, pain, or redness persists or worsens.

Keep out of reach of children.

Directions

• adults and children 5 years and over: dissolve 1 or 2 drops (one at a time) slowly in the mouth. Repeat as needed. • children under 5 years: ask a doctor.

Other information

• 15 calories per drop • contains: SOY.

Inactive ingredients

beta carotene, citric acid, FD&C blue 2, FD&C red 40, flavors, menthol, glucose syrup, lactic acid, malic acid, potassium citrate, soy lecithin, sucrose, titanium dioxide, sucralose, water.

Questions?

call 800 935 2362 Monday-Friday 9AM-5PM EST

RESEALABLE BAG

Compare to Active Ingredient of Halls®

Relieves Coughs & Soothes Sore Throats

Soothing Drops,
Starts Working In Seconds

Temporarily Relieves Cough

CLOSE BAG TO MAINTAIN FRESHNESS

CHOKING WARNING:
NOT FOR CHILDREN UNDER 4.

QC 100% SATISFACTION GUARANTEED ®

Distributed by CDMA, Inc.
Novi, MI 48375
www.qualitychoice.com
Questions: 800-935-2362

Made In China